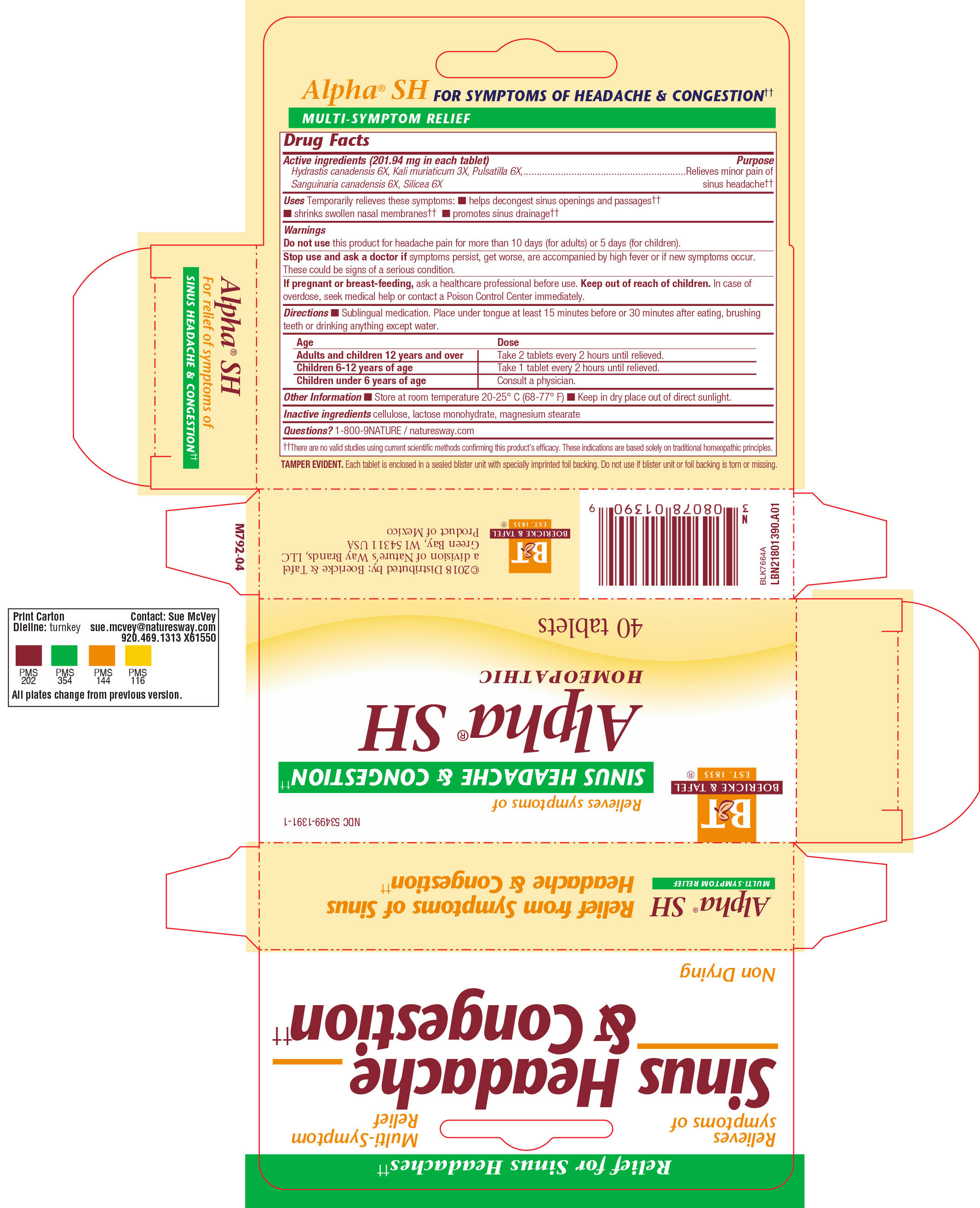 DRUG LABEL: ALPHA SH
NDC: 68466-4191 | Form: TABLET
Manufacturer: Schwabe Mexico, S.A. de C.V.
Category: homeopathic | Type: HUMAN OTC DRUG LABEL
Date: 20220322

ACTIVE INGREDIENTS: SANGUINARIA CANADENSIS ROOT 6 [hp_X]/1 1; GOLDENSEAL 6 [hp_X]/1 1; SILICON DIOXIDE 6 [hp_X]/1 1; POTASSIUM CHLORIDE 3 [hp_X]/1 1; PULSATILLA VULGARIS 6 [hp_X]/1 1
INACTIVE INGREDIENTS: LACTOSE MONOHYDRATE; MAGNESIUM STEARATE; CELLULOSE, MICROCRYSTALLINE

Alpha SH

Active Ingredient

Hydraetis canadensis 6X

Kali muriaticum 3X

Pulsatilla 6X

Sanguinaria canadensis 6X

Silcea 6X

INACTIVE INGREDIENT

Cellulose

Lactose monohydrate

Magnesium stearate

Purpose

Temporarily relieves these symptoms: helps decongest sinus openings and passages, shrinks swollen nasal membranes and promotes sinus drainage.

Indications & Usage

Temporarily relieves these symptoms: helps decongest sinus openings and sinus passages, shrinks swollen nasal membranse, promotes sinus drainage.

Dosage & Administration

Directions:
Sublingual medication. Place tablets under tongue at least 15 minutes before or 30m minutes after eating, brushing teeth, or drinking anything except water.
Adults and children 12 years of age and older: Take 2 tablets every 2 hours until relieved.
Children 2 to 12: Take 1 every 2 hours until relieved
Children under 2: Consult a physician.

Warnings

Do not use this product for headache pain for more than 10 days (for adults) or 5 days (for children).

Stop use

Stop use and ask a doctor if symptoms persist, get worse, or are accompanied by a high fever, or if new symptoms occur.
These can be signs of a serious condition.

Pregnancy or Breast Feeding

If pregnant or breast feeding, ask a healthcare professional before use.

Keep out of reach of children

Overdose

In case of overdose, seek medical help or contact a Poison Control Center immediately.